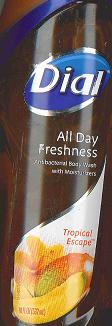 DRUG LABEL: Dial Tropical Escape Antibacterial Body Wash
NDC: 54340-180 | Form: SOLUTION
Manufacturer: The Dial Corporation
Category: otc | Type: HUMAN OTC DRUG LABEL
Date: 20110418

ACTIVE INGREDIENTS: TRICLOSAN 0.15 mL/1000 mL
INACTIVE INGREDIENTS: WATER; SODIUM LAURETH SULFATE; COCAMIDOPROPYL BETAINE; SODIUM CHLORIDE; DMDM HYDANTOIN; EDETATE SODIUM; CITRIC ACID MONOHYDRATE; POLYETHYLENE GLYCOL 400; GLYCERIN; POLYQUATERNIUM-10 (400 CPS AT 2%); CHLORIDE ION; MORPHOLINE; LACTIC ACID; FD&C RED NO. 4; FD&C YELLOW NO. 5

Drug Facts

Active Ingredient - Triclosan 0.15%

PURPOSE

Antibacterial

INDICATIONS AND USAGE

For hand washing to decrease bacteria on the skin

WARNINGS

For external use only

WHEN USING

Avoid contact with eyes. In case of eye contact, flush with water.

Stop use and ask a doctor if irritation and redness develops.

Keep out of reach of children. If swallowed, get medical help or contact a Poison Control Center right away.

Directions

- Squeeze onto hands or body sponge
- Work into lather
- Wash skin, rinse thoroughly and dry

INACTIVE INGREDIENT

Water, sodium laureth sulfate, cocamidopropyl betaine, PEG-8, fragrance, glycerin, polyquaternium-10, cocamidopropyl PG-dimonium chloride, isostearamidopropyl morpholine lactate, sodium chloride, DMDM hydantoin, citric acid, tetrasodium EDTA, red 4, yellow 5.

Questions? 1-800-258-DIAL (3425)